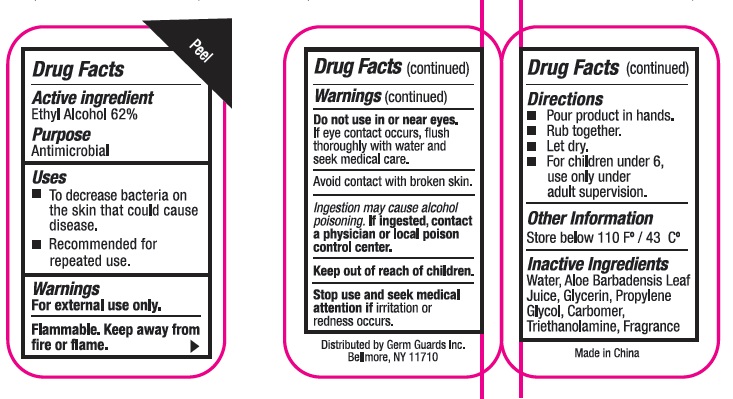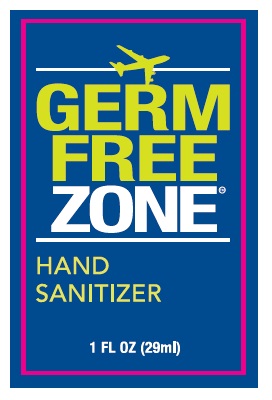 DRUG LABEL: Hand Sanitizer
NDC: 71089-002 | Form: GEL
Manufacturer: Germ Guards Incorporated
Category: otc | Type: HUMAN OTC DRUG LABEL
Date: 20170601

ACTIVE INGREDIENTS: ALCOHOL 62 mL/100 mL
INACTIVE INGREDIENTS: WATER; ALOE VERA LEAF; GLYCERIN; PROPYLENE GLYCOL; CARBOMER INTERPOLYMER TYPE A (55000 CPS); TROLAMINE

Active Ingredient
Ethyl Alcohol 62%

Purpose
Antimicrobial

Warnings

For external use only.

Flammable. Keep away from fire or flame.

Do not use in or near eyes. If eye contact occurs, flush thoroughly with water and seek medical care.

Avoid contact with broken skin.

Ingestion may cause alcohol poisoning. If ingested, contact a physician or local poison control center.

Stop use and seek medical attention if irritation or redness occurs.

Keep out of reach of children.

Directions

- Pour product in hands.
- Rub together
- Let dry
- For children under 6, use only under adult supervision.

INACTIVE INGREDIENT

Inactive Ingredients: Water, Aloe Barbadenis Leaf Juice, Glycerin, Propylene Glycol, Carbomer, Triethanolamine, Fragrance

Uses

- To decrease bacteria on the skin that could cause disease.
- Recommended for repeated use.

Other Information

Store below 110 F/43 C